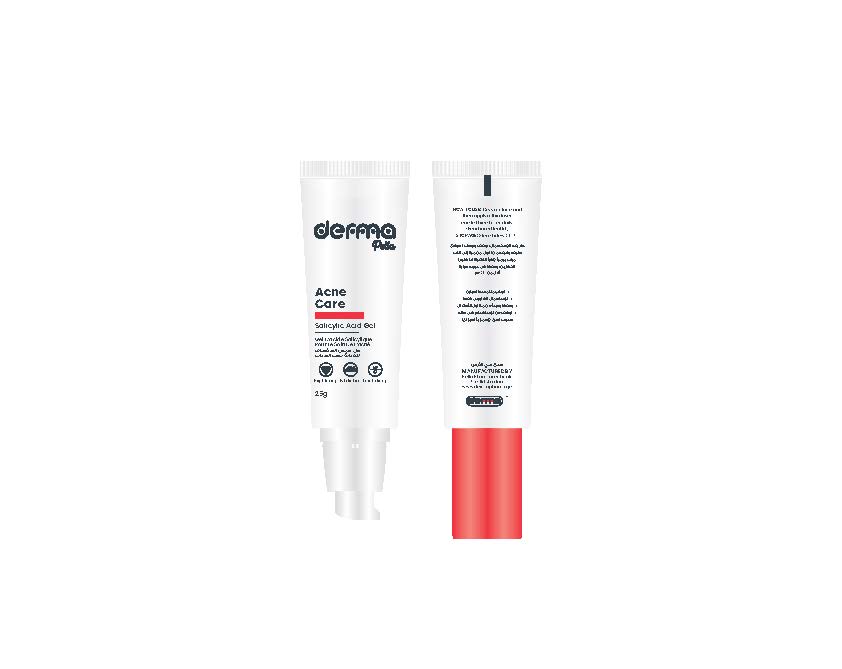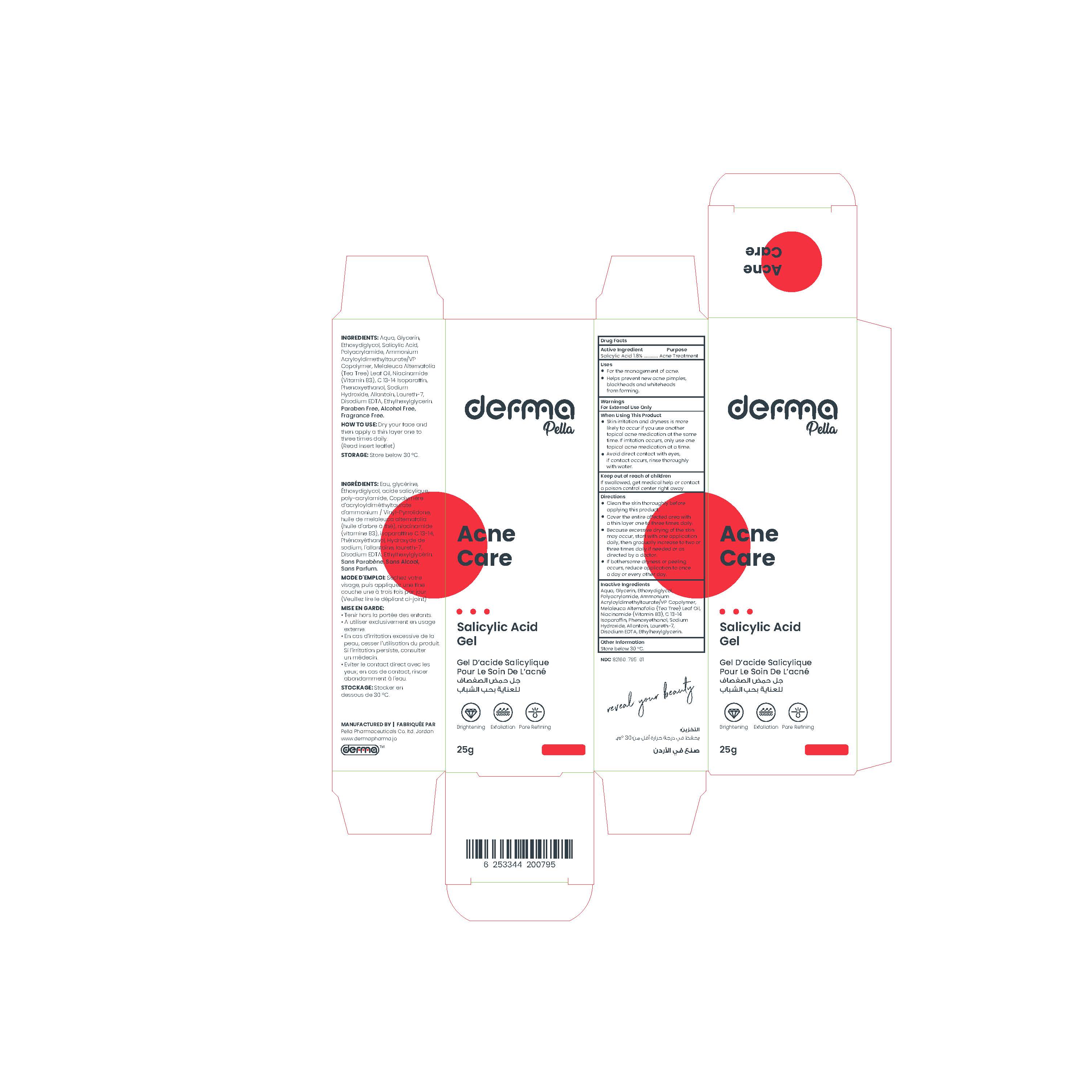 DRUG LABEL: Derma Pella Acne Care
NDC: 82160-795 | Form: GEL
Manufacturer: Pella Pharmaceuticals Co. Ltd
Category: otc | Type: HUMAN OTC DRUG LABEL
Date: 20240201

ACTIVE INGREDIENTS: SALICYLIC ACID 18 mg/1 g
INACTIVE INGREDIENTS: WATER; GLYCERIN; LAURETH-7; ETHYLHEXYLGLYCERIN; EDETATE DISODIUM ANHYDROUS; TEA TREE OIL; NIACINAMIDE; SODIUM HYDROXIDE; DIETHYLENE GLYCOL MONOETHYL ETHER; ALLANTOIN; PHENOXYETHANOL; AMMONIUM ACRYLOYLDIMETHYLTAURATE/VP COPOLYMER; C13-14 ISOPARAFFIN

Acne Care Gel

Form and Presentation

Gel: Plastic Tube, 25 g

Active Ingredient

Salicylic Acid

Inactive Ingredients

Aqua, Glycerin, Ethoxydiglycol, Polyacrylamide, Ammonium Acryloyldimethyltaurate/VP Copolymer, Melaleuca Alternafolia (Tea Tree) Leaf Oil, Niacinamide (Vitamin B3), C 13-14 Isoparaffin, Phenoxyethanol, Sodium Hydroxide, Allantoin, Laureth-7, Disodium EDTA, Ethylhexylglycerin.

Purpose

Acne care gel

Properties

A lightweight, water-based alcohol-free gel.
This product contains a beta hydroxyl acid (BHA) which is a salicylic acid that clears out clogged pores, reduces blemishes, and helps to minimize blackheads and breakouts. It dissolves excess sebum, making it suitable for acne-prone skin.
And also, it contains Tea tree oil which has soothing properties and improves the appearance of marks.
In addition to Niacinamide (Vitamin B3) which works best to soothe and lighten skin, visibly minimize pores, and improve uneven skin tone, reduce dark spots and acne spots.
It contains Allantoin which is an effective moisturizing ingredient used for it is gentle and non-irritating qualities.
Paraben free, Alcohol free, Fragrance free.

Indications

Helps to clear acne and reduce formation of new blackheads and whiteheads.

Precautions

Keep out of reach of children

Warnings

- For external use only.
- Discontinue if excessive skin irritation develops or increases. If irritation persists, consult with a physician or pharmacist.
- Avoid direct contact with eyes, if contact occurs, rinse thoroughly with water.

Contraindications

Hypersensitivity to any of the components.

Side Effects

Skin irritations, dryness, redness more likely to occur when using another topical acne product at the same time, if irritation occurs, use only one product at a time.

Dosage and Administration

- Cleanse skin thoroughly before applying product.
- Dry your face and then apply a thin layer one to three times daily.
- Because excessive drying of the skin may occur, start with one application daily, and then gradually increase to two or three times daily, if needed.
- If bothersome dryness or peeling occurs, reduce application to once a day or every other day.

Storage Conditions

Store below 30◦C.